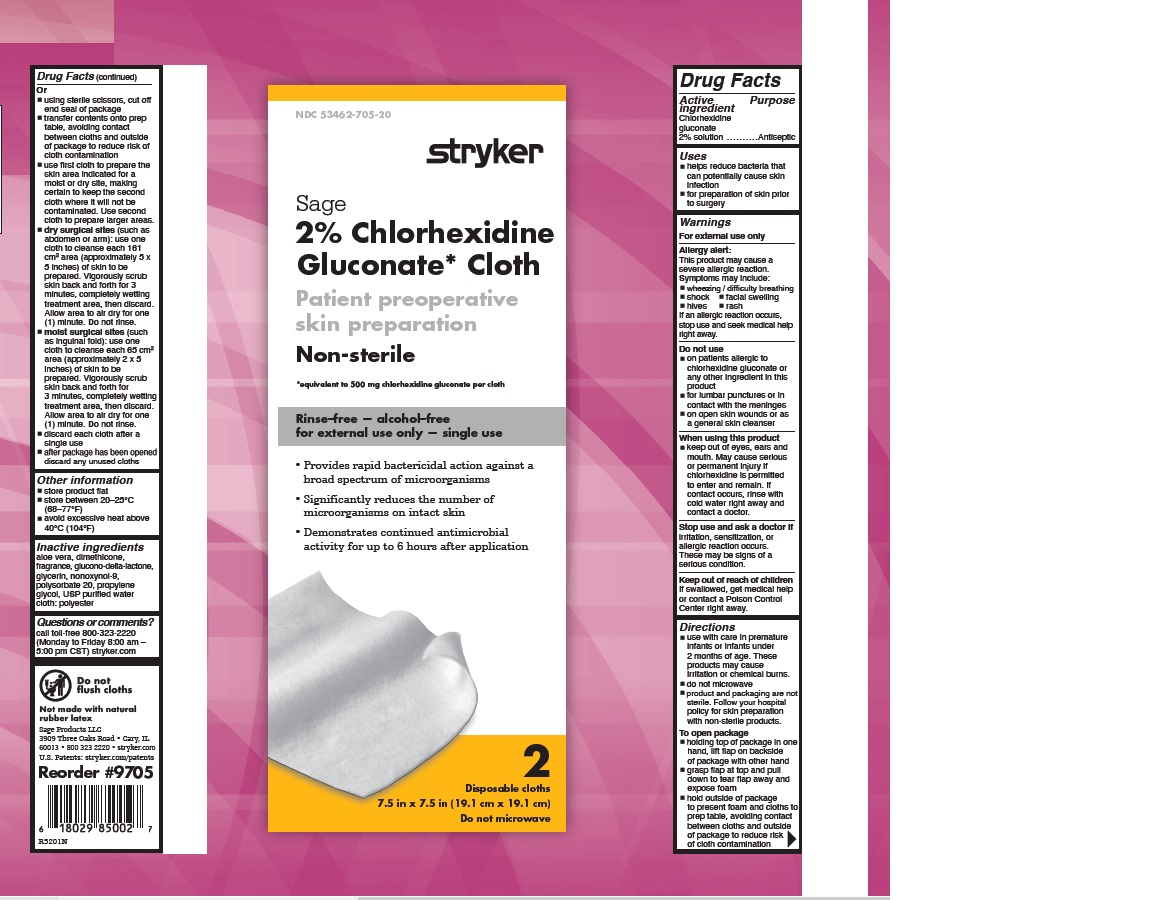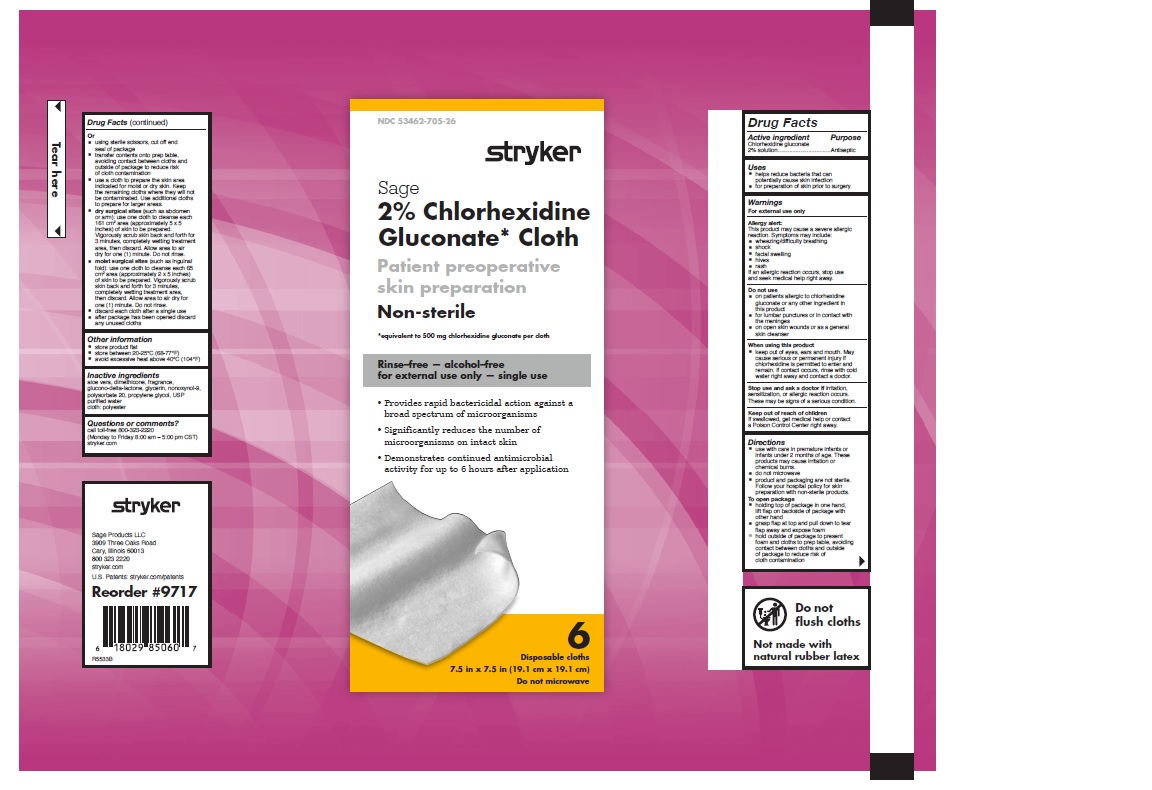 DRUG LABEL: CHLORHEXIDINE GLUCONATE
NDC: 53462-705 | Form: CLOTH
Manufacturer: Sage Products LLC
Category: otc | Type: HUMAN OTC DRUG LABEL
Date: 20251212

ACTIVE INGREDIENTS: CHLORHEXIDINE GLUCONATE 500 mg/1 1
INACTIVE INGREDIENTS: WATER; NONOXYNOL-9; POLYSORBATE 20; DIMETHICONE 350; PROPYLENE GLYCOL; ALOE VERA LEAF; GLYCERIN; GLUCONOLACTONE

Chlorhexidine Gluconate 2% Solution

2% CHLORHEXIDINE GLUCONATE CLOTH

Active Ingredient | Purpose
Chlorhexidine Gluconate 2% Solution | Antiseptic

Uses

- helps reduce bacteria that can potentially cause skin infection
- for preparation of skin prior to surgery

Warnings

For external use only

Allergy alert:

This product may cause a severe allergic reaction. Symptoms may include:

- wheezing/difficulty breathing
- shock
- facial swelling
- hives
- rash

If an allergic reaction occurs, stop use and seek medical help right away.

Do not use

- on patients allergic to chlorhexidine gluconate or any other ingredient in this product
- for lumbar punctures or in contact with the meninges
- on open skin wounds or as a general skin cleanser

When using this product

- keep out of eyes, ears and mouth. May cause serious or permanent injury if chlorhexidine is permitted to enter and remain. If contact occurs, rinse with cold water right away and contact a doctor.

Stop use and ask a doctor if irritation, sensitization or allergic reaction occurs. These may be signs of a serious condition.

Keep out of reach of children

If swallowed, get medical help or contact a Poison Control Center right away.

Directions

- use with care in premature infants or infants under 2 months of age. These products may cause irritation or chemical burns.
- do not microwave
- product and packaging are not sterile. Follow your hospital policy for skin preparation with non-sterile products.

To open package

- holding top of package in one hand, lift flap on backside of package with other hand
- grasp flap at top and pull down to tear flap away and expose foam
- hold outside of package to present foam and cloths to prep table, avoiding contact between cloths and outside of package to reduce risk of cloth contamination

Or

- using sterile scissors, cut off end seal of package
- transfer contents onto prep table, avoiding contact between cloths and outside of package to reduce risk of cloth contamination
- use first cloth to prepare the skin area indicated for a moist or dry site, making certain to keep the second cloth where it will not be contaminated. Use second cloth to prepare larger areas.
- dry surgical sites (such as abdomen or arm): use one cloth to cleanse each 161 cm^2 area (approximately 5 x 5 inches) of skin to be prepared. Vigorously scrub skin back and forth for 3 minutes, completely wetting treatment area, then discard. Allow area to air dry for one (1) minute. Do not rinse.
- moist surgical sites (such as inguinal fold): use one cloth to cleanse each 65 cm^2 area (approximately 2 x 5 inches) of skin to be prepared. Vigorously scrub skin back and forth for 3 minutes, completely wetting treatment area, then discard. Allow area to air dry for one (1) minute. Do not rinse.
- discard each cloth after a single use
- after package has been opened discard any unused cloths

Other information

store product flat
store between 20-25°C (68-77°F)
avoid excessive heat above 40°C (104°F)

Inactive Ingredients

aloe vera, dimethicone, fragrance, glucono-delta-lactone, glycerin, nonoxynol-9, polysorbate 20, propylene glycol, USP purified water

cloth: polyester

Questions or comments?

call toll-free 800-323-2220

(Monday to Friday 8 AM - 5 PM CST)

www.sageproducts.com

DO NOT FLUSH CLOTHS

Not made with natural rubber latex

Patents:

www.sageproducts.com/patents